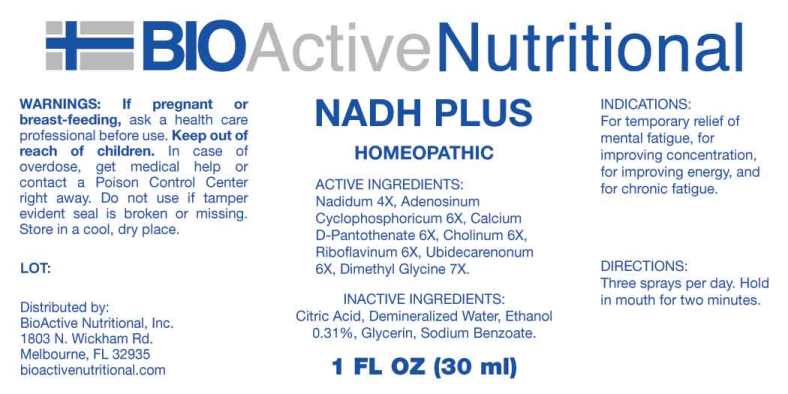 DRUG LABEL: NADH Plus
NDC: 43857-0023 | Form: SPRAY
Manufacturer: BioActive Nutritional
Category: homeopathic | Type: HUMAN OTC DRUG LABEL
Date: 20231211

ACTIVE INGREDIENTS: NADIDE 4 [hp_X]/1 mL; ADENOSINE CYCLIC PHOSPHATE 6 [hp_X]/1 mL; CALCIUM PANTOTHENATE 6 [hp_X]/1 mL; CHOLINE HYDROXIDE 6 [hp_X]/1 mL; RIBOFLAVIN 6 [hp_X]/1 mL; UBIDECARENONE 6 [hp_X]/1 mL; N,N-DIMETHYLGLYCINE 7 [hp_X]/1 mL
INACTIVE INGREDIENTS: CITRIC ACID MONOHYDRATE; WATER; GLYCERIN; SODIUM BENZOATE; ALCOHOL

DRUG FACTS:

ACTIVE INGREDIENTS:

Nadidum 4X, Adenosinum Cyclophosphoricum 6X, Calcium D-Pantothenate 6X, Cholinum 6X, Riboflavinum 6X, Ubidecarenonum 6X, Dimethyl Glycine 7X.

INDICATIONS:

For temporary relief of mental fatigue, for improving concentration, for improving energy, and for chronic fatigue.

WARNINGS:

If pregnant or breast-feeding, ask a health care professional before use.

Keep out of reach of children. In case of overdose, get medical help or contact a Poison Control Center right away.

Do not use if tamper evident seal is broken or missing.

Store in a cool, dry place.

Keep out of reach of children. In case of overdose, get medical help or contact a Poison Control Center right away.

DIRECTIONS:

Three sprays per day. Hold in mouth for two minutes.

INDICATIONS:

For temporary relief of mental fatigue, for improving concentration, for improving energy and for chronic fatigue.

INACTIVE INGREDIENTS:

Citric Acid, Demineralized Water, Ethanol 0.31%, Glycerin, Sodium Benzoate.

QUESTIONS:

Distributed by:
BioActive Nutritional, Inc.
1803 N. Wickham Rd.
Melbourne, FL 32935
bioactivenutritional.com

PACKAGE LABEL DISPLAY:

BIOActive Nutritional

NADH PLUS

HOMEOPATHIC

1 FL OZ (30 ml)